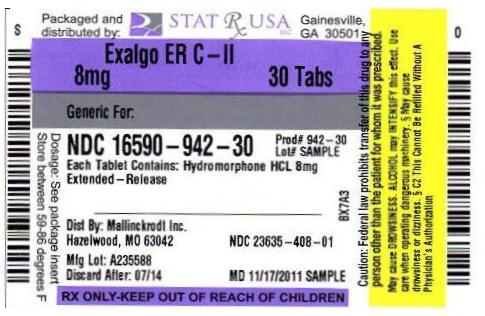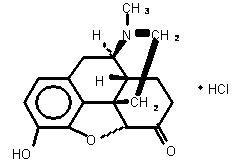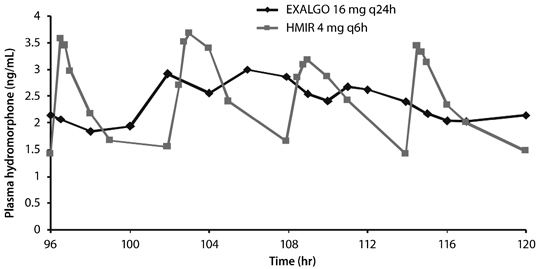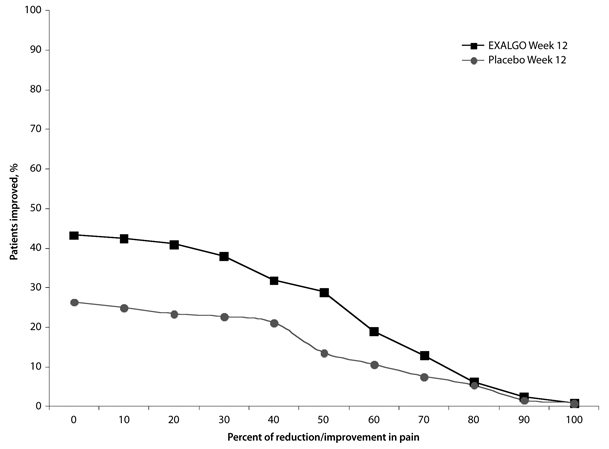 DRUG LABEL: EXALGO
NDC: 16590-942 | Form: TABLET, EXTENDED RELEASE
Manufacturer: STAT Rx USA LLC
Category: prescription | Type: HUMAN PRESCRIPTION DRUG LABEL
Date: 20111129
DEA Schedule: CII

ACTIVE INGREDIENTS: HYDROMORPHONE HYDROCHLORIDE 8 mg/1 1
INACTIVE INGREDIENTS: BUTYLATED HYDROXYTOLUENE; CELLULOSE ACETATE; FERROSOFERRIC OXIDE; FERRIC OXIDE RED; HYPROMELLOSE 2910 (5 MPA.S); LACTOSE, ANHYDROUS; LACTOSE MONOHYDRATE; MAGNESIUM STEARATE; POLYETHYLENE GLYCOL; POVIDONE; SODIUM CHLORIDE; TITANIUM DIOXIDE; TRIACETIN

HIGHLIGHTS OF PRESCRIBING INFORMATION

These highlights do not include all the information needed to use EXALGO™ safely and effectively. See full prescribing information for EXALGO.
EXALGO (hydromorphone HCl) Extended-Release Tablets, CII
Initial U.S. Approval: 1984

WARNING: POTENTIAL FOR ABUSE, IMPORTANCE OF PROPER PATIENT SELECTION AND LIMITATIONS OF USE

WARNING: POTENTIAL FOR ABUSE, IMPORTANCE OF PROPER PATIENT SELECTION AND LIMITATIONS OF USESee full prescribing information for complete boxed warning.

- EXALGO is indicated for opioid tolerant patients only (1).
- EXALGO contains hydromorphone, a Schedule II controlled substance, which can be abused and is subject to misuse, abuse, addiction, and criminal diversion (9).
- EXALGO is not indicated for use in the management of acute or postoperative pain and is not intended for use as an as-needed analgesic (4).
- Fatal respiratory depression could occur in patients who are not opioid tolerant (5).
- Accidental consumption of EXALGO, especially in children, can result in a fatal overdose of hydromorphone (5).
- EXALGO tablets are to be swallowed whole and are not to be broken, chewed, dissolved, crushed or injected. Taking broken, chewed, dissolved or crushed EXALGO leads to rapid release and absorption of a potentially fatal dose of hydromorphone (5).

1 INDICATIONS AND USAGE

- EXALGO is an opioid agonist indicated for once daily administration for the management of moderate to severe pain in opioid tolerant patients requiring continuous, around-the-clock opioid analgesia for an extended period of time (1).
- EXALGO is NOT intended for use as an as-needed analgesic (1).

2 DOSAGE AND ADMINISTRATION

- Dosage: Dose range studied in clinical trials is 8 mg to 64 mg once-daily (2.1).

3 DOSAGE FORMS AND STRENGTHS

- Tablets: 8 mg, 12 mg or 16 mg dosage strengths (3)

4 CONTRAINDICATIONS

- Opioid non-tolerant patients (4.1)
- Impaired pulmonary function (4.2)
- Paralytic ileus (4.3)
- Narrowed or obstructed gastrointestinal tract (4.4)
- Known hypersensitivity to any components including hydromorphone hydrochloride and sulfites (4.5, 5.8)

5 WARNINGS AND PRECAUTIONS

- EXALGO can be abused. Use caution when prescribing if there is an increased risk of misuse, abuse, or diversion (5.2).
- EXALGO may be associated with clinically significant respiratory depression. Monitor patients accordingly (5.3).
- EXALGO may have additive effects when used in conjunction with alcohol and other CNS depressants (5.4). Use EXALGO with extreme caution in patients susceptible to intracranial effects of CO2 retention (5.5).
- EXALGO may cause hypotension. Use with caution in patients in circulatory shock (5.6).
- EXALGO should not be abruptly discontinued (5.13).

6 ADVERSE REACTIONS

Most common adverse reactions (>10%) are: constipation, nausea, vomiting, somnolence, headache, and dizziness (6.1).

To report SUSPECTED ADVERSE REACTIONS, contact Covidien at 1-800-778-7898 or FDA at 1-800-FDA-1088 or www.fda.gov/medwatch.

7 DRUG INTERACTIONS

- EXALGO is not intended for patients taking Monoamine oxidase (MAO) inhibitors or within 14 days of stopping such treatment (7).
- Mixed agonist/antagonist opioid analgesics may reduce the analgesic effect of EXALGO and/or may precipitate withdrawal symptoms (7.3).
- Medications with anticholinergic activity when used with EXALGO may increase risk of urinary retention and/or severe constipation (7.4).

8 USE IN SPECIFIC POPULATIONS

- EXALGO is not recommended during labor and delivery, pregnancy, or nursing (8.1, 8.2, 8.3).
- Administer EXALGO with caution, and in reduced dosages in elderly patients (8.5).
- Administer a reduced dose of EXALGO in patients with moderate and severe hepatic (8.7) and moderate renal impairment (8.8). Consider use of an alternate analgesic in patients with severe renal impairment (8.8).

FULL PRESCRIBING INFORMATION

WARNING: POTENTIAL FOR ABUSE, IMPORTANCE OF PROPER PATIENT SELECTION AND LIMITATIONS OF USE

Potential for Abuse
EXALGO contains hydromorphone, an opioid agonist and a Schedule II controlled substance with an abuse liability similar to other opioid analgesics. EXALGO can be abused in a manner similar to other opioid agonists, legal or illicit. These risks should be considered when administering, prescribing, or dispensing EXALGO in situations where the healthcare professional is concerned about increased risk of misuse, abuse, or diversion. Schedule II opioid substances which include hydromorphone, morphine, oxycodone, fentanyl, oxymorphone and methadone have the highest potential for abuse and risk of fatal overdose due to respiratory depression [see Drug Abuse and Dependence (9)].

Proper Patient Selection
EXALGO is an extended-release formulation of hydromorphone hydrochloride indicated for the management of moderate to severe pain in opioid tolerant patients when a continuous around-the-clock opioid analgesic is needed for an extended period of time. Patients considered opioid tolerant are those who are taking at least 60 mg oral morphine per day, 25 mcg transdermal fentanyl/hour, 30 mg oral oxycodone/day, 8 mg oral hydromorphone/day, 25 mg oral oxymorphone/day or an equianalgesic dose of another opioid, for a week or longer [see Indications and Usage (1) and Dosage and Administration (2)].

EXALGO is for use in opioid tolerant patients only [see Indications and Usage (1) and Dosage and Administration (2)].

Fatal respiratory depression could occur in patients who are not opioid tolerant.

Accidental consumption of EXALGO, especially in children, can result in a fatal overdose of hydromorphone [see Warnings and Precautions (5.1)].

Limitations of Use
EXALGO is not indicated for the management of acute or postoperative pain [see Indications and Usage (1)].

EXALGO is not intended for use as an as-needed analgesic [see Indications and Usage (1)].

EXALGO tablets are to be swallowed whole and are not to be broken, chewed, dissolved, crushed or injected. Taking broken, chewed, dissolved or crushed EXALGO or its contents leads to rapid release and absorption of a potentially fatal dose of hydromorphone [see Warnings and Precautions (5)].

1 INDICATIONS AND USAGE

EXALGO is an extended-release oral formulation of hydromorphone hydrochloride indicated for the management of moderate to severe pain in opioid tolerant patients requiring continuous, around-the-clock opioid analgesia for an extended period of time.

Patients considered opioid tolerant are those who are taking at least 60 mg oral morphine per day, 25 mcg transdermal fentanyl/hour, 30 mg oral oxycodone/day, 8 mg oral hydromorphone/day, 25 mg oral oxymorphone/day or an equianalgesic dose of another opioid, for a week or longer.

EXALGO is NOT intended for use as an as-needed analgesic.

EXALGO is not indicated for the management of acute or postoperative pain.

2 DOSAGE AND ADMINISTRATION

Selection of patients for treatment with EXALGO is governed by the same principles that apply to the use of similar opioid analgesics. Physicians should individualize treatment in every case, using non-opioid analgesics, opioids on an as-needed basis and/or combination products, and chronic opioid therapy in a progressive plan of pain management such as the guidelines outlined by the World Health Organization or the Federation of State Medical Boards Model Guidelines.

EXALGO should be swallowed whole and should not be broken, crushed, dissolved, or chewed before swallowing.

2.1 Conversion to EXALGO in Opioid Tolerant Patients

The dose range of EXALGO studied in clinical trials is 8 mg to 64 mg. The tablets are to be administered every 24 hours with or without food. Discontinue all other extended-release opioids when beginning EXALGO therapy. As EXALGO is only for use in opioid tolerant patients, do not begin any patient on EXALGO as the first opioid.

Use caution to avoid medication errors when prescribing or dispensing EXALGO 8 mg tablets, as 8 mg tablets are also available as immediate-release hydromorphone tablets.

It is critical to initiate the dosing regimen individually for each patient. Overestimating the EXALGO dose when converting patients from another opioid medication can result in fatal overdose with the first dose [see Overdosage (10)].

In the selection of the initial dose of EXALGO, give attention to the following:

- the daily dose, potency, and specific characteristics of the opioid the patient has been taking previously;
- the reliability of the relative potency estimate used to calculate the equivalent hydromorphone dose needed;
- the patient's degree of opioid tolerance;
- the age, general condition, and medical status of the patient;
- concurrent non-opioid analgesics and other medications, such as those with Central Nervous System (CNS) activity [see Drug Interactions (7)];
- the type and severity of the patient's pain;
- the balance between pain control and adverse effects;
- risk factors for abuse, addiction, or diversion, including a prior history of abuse, addiction, or diversion.

The following dosing recommendations, therefore, can only be considered as suggested approaches to what is actually a series of clinical decisions over time in the management of the pain of each individual patient.

Conversion from Other Oral Hydromorphone Formulations to EXALGO
Patients receiving oral immediate-release hydromorphone may be converted to EXALGO by administering a starting dose equivalent to the patient’s total daily oral hydromorphone dose, taken once daily. The dose of EXALGO can be titrated every 3 to 4 days until adequate pain relief with tolerable side effects has been achieved [see Dosage and Administration (2.1)].

Conversion from Oral Opioids to EXALGO
For conversion from other opioids to EXALGO, physicians and other healthcare professionals are advised to refer to published relative potency information, keeping in mind that conversion ratios are only approximate. In general, start EXALGO therapy by administering 50% of the calculated total daily dose of EXALGO (see conversion ratio table below) every 24 hours. The initial dose of EXALGO can be titrated until adequate pain relief with tolerable side effects has been achieved. The following table provides approximate equivalent doses, which may be used as a guideline for conversion.

- The conversion ratios and approximate equivalent doses in this conversion table (Table 1) are only to be used for the conversion from current oral opioid therapy to EXALGO. No fixed conversion ratio is likely to be satisfactory in all patients, especially in patients receiving large opioid doses.
- For patients on a regimen of mixed opioids, calculate the approximate oral hydromorphone dose for each opioid and sum the totals.
- For patients on a regimen of fixed-ratio opioid/non-opioid analgesic medications, only the opioid component of these medications should be used in the conversion. The non-opioid component may be continued as a separate drug, or a different non-opioid analgesic may be selected.
- There is substantial patient variation in the relative potency of different opioid drugs and formulations.
- It is extremely important to monitor all patients closely when converting from methadone to other opioid agonists. The ratio between methadone and other opioid agonists may vary widely as a function of previous dose exposure. Methadone has a long half-life and tends to accumulate in the plasma.
- The recommended doses are only a starting point, and close observation and titration are indicated until a satisfactory dose is obtained on the new therapy.

Table 1. Conversion Ratios to EXALGO [The conversion ratios and approximate equivalent doses in this conversion table are only to be used for the conversion from current opioid therapy to EXALGO.]
Previous Opioid | Approximate Equivalent Oral Dose | Oral Conversion Ratio [Ratio for conversion of oral opioid dose to approximate hydromorphone equivalent dose.]
Hydromorphone | 12 mg | 1
Codeine | 200 mg | 0.06
Hydrocodone | 30 mg | 0.4
Methadone [It is extremely important to monitor all patients closely when converting from methadone to other opioid agonists. The ratio between methadone and other opioid agonists may vary widely as a function of previous dose exposure. Methadone has a long half-life and tends to accumulate in the plasma.] | 20 mg | 0.6
Morphine | 60 mg | 0.2
Oxycodone | 30 mg | 0.4
Oxymorphone | 20 mg | 0.6

Select opioid, sum the total daily dose, and then multiply the dose by the conversion ratio to calculate the approximate oral hydromorphone equivalent.

Conversion from Transdermal Fentanyl to EXALGO
Eighteen hours following the removal of the transdermal fentanyl patch, EXALGO treatment can be initiated. For each 25 mcg/hr fentanyl transdermal dose the equianalgesic dose of EXALGO is 12 mg every 24 hours. An appropriate starting dose of EXALGO is 50% of the calculated total daily dose every 24 hours.

Individualization of Dosage

- Once therapy is initiated, assess pain relief and other opioid adverse reactions frequently.
- Titrate patients to adequate analgesia with dose increases not more often than every 3 to 4 days, in order to attain steady-state plasma concentrations of hydromorphone at each dose.
- As a guideline, consider dosage increases of 25% to 50% of the current daily dose of EXALGO for each titration step.
- If more than two doses of rescue medication are needed within a 24 hour period for two consecutive days, the dose of EXALGO may need to be titrated upward.
- Administer EXALGO no more frequently than every 24 hours.

During periods of changing analgesic requirements, including initial titration, maintain frequent contact between physician, other members of the healthcare team, the patient and the caregiver/family.

2.2 Maintenance of Therapy

During chronic therapy with EXALGO, assess the continued need for around-the-clock opioid therapy periodically. Continue to assess patients for their clinical risks for opioid abuse, addiction, or diversion particularly with high-dose formulations. If patients need to titrate while on maintenance therapy, follow the same method outlined in Individualization of Dosage to re-establish pain control.

2.3 Discontinuation of EXALGO

When the patient no longer requires therapy with EXALGO, taper doses gradually, by 25 to 50% every 2 or 3 days down to a dose of 8 mg before discontinuation of therapy, to prevent signs and symptoms of withdrawal in the physically dependent patient.

2.4 Renal and Hepatic Impairment

Start patients with moderate and severe hepatic and moderate renal impairment on a reduced dose and closely monitor during dose titration. As EXALGO is only intended for once daily administration, consider use of an alternate analgesic that may permit more flexibility with the dosing interval in patients with severe renal impairment.

3 DOSAGE FORMS AND STRENGTHS

EXALGO is available in 8 mg, 12 mg or 16 mg dosage strengths. The 8 mg tablets are round, biconvex, red tablets imprinted with "EXH 8" on one side. The 12 mg tablets are round, biconvex, dark yellow tablets imprinted with "EXH 12" on one side. The 16 mg tablets are round, biconvex, yellow tablets imprinted with "EXH 16" on one side.

4 CONTRAINDICATIONS

4.1 Opioid Non-Tolerant Patients

EXALGO is contraindicated in opioid non-tolerant patients. Fatal respiratory depression could occur in patients who are not opioid tolerant.

4.2 Impaired Pulmonary Function

EXALGO is contraindicated in patients with significant respiratory depression, especially in the absence of resuscitative equipment or in unmonitored settings and in patients with acute or severe bronchial asthma or hypercarbia.

4.3 Paralytic Ileus

EXALGO is contraindicated in patients who have or are suspected of having a paralytic ileus.

4.4 Preexisting Gastrointestinal (GI) Surgery or Narrowing of GI Tract

EXALGO is contraindicated in patients who have had surgical procedures and/or underlying disease that would result in narrowing of the gastrointestinal tract, or have “blind loops” of the gastrointestinal tract or gastrointestinal obstruction.

4.5 Allergy or Hypersensitivity

EXALGO is contraindicated in patients with known hypersensitivity to any of its components including the active agent, hydromorphone hydrochloride or known allergy to sulfite-containing medications [see Warnings and Precautions (5.8)].

5 WARNINGS AND PRECAUTIONS

5.1 Information Essential for Safe Administration

EXALGO tablets are to be swallowed whole, and are not to be broken, chewed, crushed, dissolved or injected. Taking broken, chewed, crushed, dissolved EXALGO or its contents leads to the rapid release and absorption of a potentially fatal dose of hydromorphone [see Boxed Warning].

EXALGO is for use only in opioid tolerant patients. Ingestion of EXALGO may cause fatal respiratory depression when administered to patients who are not opioid tolerant [see Boxed Warning].

EXALGO tablets must be kept in a secure place out of the reach of children. Accidental consumption of EXALGO, especially in children, can result in a fatal overdose of hydromorphone.

5.2 Misuse and Abuse

EXALGO contains hydromorphone, an opioid agonist, and is a Schedule II controlled substance. Opioid agonists have the potential for being abused and are sought by drug abusers and people with addiction disorders and are subject to criminal diversion.

EXALGO can be abused in a manner similar to other opioid agonists, legal or illicit. This should be considered when prescribing or dispensing EXALGO in situations where the healthcare professional is concerned about an increased risk of misuse, abuse, or diversion.

Breaking, crushing, chewing, or dissolving the contents of an EXALGO tablet results in the uncontrolled delivery of the opioid and poses a significant risk of overdose and death [see Drug Abuse and Dependence (9)].

If attempts are made to extract the drug from the hard outer shell for purposes of parenteral abuse, the injection of tablet excipients may be toxic and may result in lethal complications.

Concerns about abuse, addiction, and diversion should not prevent the proper management of pain. However, all patients treated with opioids, including EXALGO, require careful monitoring for signs of abuse and addiction, since use of opioid analgesic products carries the risk of addiction even under appropriate medical use.

Healthcare professionals should contact their State Professional Licensing Board or State Controlled Substances Authority for information on how to prevent and detect abuse or diversion of this product.

5.3 Respiratory Depression

Respiratory depression is the chief hazard of EXALGO. Respiratory depression occurs more frequently in elderly or debilitated patients as well as those suffering from conditions accompanied by hypoxia or hypercapnia when even moderate therapeutic doses may dangerously decrease pulmonary ventilation, and when opioids are given in conjunction with other agents that depress respiration.

Use EXALGO with extreme caution in patients with conditions accompanied by hypoxia, hypercapnia, or decreased respiratory reserve such as asthma, chronic obstructive pulmonary disease or cor pulmonale, severe obesity, sleep apnea, myxedema, kyphoscoliosis or CNS depression. In these patients, even moderate therapeutic doses of hydromorphone may decrease respiratory drive while simultaneously increasing airway resistance to the point of apnea. In these patients, consider alternative non-opioid analgesics, and use EXALGO only under careful medical supervision at the lowest effective dose.

5.4 Interactions with Alcohol and Other CNS Depressants

The concurrent use of EXALGO with other central nervous system (CNS) depressants, including but not limited to other opioids, illicit drugs, sedatives, hypnotics, general anesthetics, phenothiazines, muscle relaxants, other tranquilizers, and alcohol, increases the risk of respiratory depression, hypotension, and profound sedation, potentially resulting in coma or death. Use with caution and in reduced dosages in patients taking CNS depressants. Avoid concurrent use of alcohol and EXALGO [see Clinical Pharmacology (12.3)].

5.5 Head Injury and Increased Intracranial Pressure

In the presence of head injury, intracranial lesions or a preexisting increase in intracranial pressure, the respiratory depressant effects of EXALGO and its potential to elevate cerebrospinal fluid pressure (resulting from vasodilation following CO2 retention) may be markedly exaggerated. Furthermore, EXALGO can produce effects on pupillary response and consciousness, which may obscure neurologic signs of further increases in intracranial pressure in patients with head injuries.

5.6 Hypotensive Effect

EXALGO may cause severe hypotension. There is added risk to individuals whose ability to maintain blood pressure has been compromised by a depleted blood volume, or after concurrent administration with drugs such as phenothiazines, general anesthetics, or other agents that compromise vasomotor tone.

Administer EXALGO with caution to patients in circulatory shock, since vasodilation produced by the drug may further reduce cardiac output and blood pressure.

5.7 Gastrointestinal Effects

Because the EXALGO tablet is nondeformable and does not appreciably change in shape in the GI tract, do not administer EXALGO to patients with preexisting severe gastrointestinal narrowing (pathologic or iatrogenic, for example: esophageal motility disorders small bowel inflammatory disease, “short gut” syndrome due to adhesions or decreased transit time, past history of peritonitis, cystic fibrosis, chronic intestinal pseudoobstruction, or Meckel’s diverticulum). There have been reports of obstructive symptoms in patients with known strictures or risk of strictures, such as previous GI surgery, in association with the ingestion of drugs in nondeformable extended-release formulations.

The administration of EXALGO may obscure the diagnosis or clinical course in patients with acute abdominal condition.

It is possible that EXALGO tablets may be visible on abdominal x-rays under certain circumstances, especially when digital enhancing techniques are utilized.

5.8 Sulfites

EXALGO contains sodium metabisulfite, a sulfite that may cause allergic-type reactions including anaphylactic symptoms and life-threatening or less severe asthmatic episodes in certain susceptible people. The overall prevalence of sulfite sensitivity in the general population is unknown and probably low. Sulfite sensitivity is seen more frequently in asthmatic than in nonasthmatic people.

5.9 MAO Inhibitors

EXALGO is not recommended for use in patients who have received MAO inhibitors within 14 days, because severe and unpredictable potentiation by MAO inhibitors has been reported with opioid analgesics.

5.10 Special Risk Groups

EXALGO should be administered with caution in elderly (≥ 65 years) and debilitated patients and in patients who are known to be sensitive to central nervous system depressants, such as those with cardiovascular, pulmonary, renal, or hepatic disease [see Use in Specific Populations (8)].

EXALGO should also be used with caution in the following conditions: adrenocortical insufficiency (e.g., Addison's disease); delirium tremens; myxedema or hypothyroidism; prostatic hypertrophy or urethral stricture; and, toxic psychosis. EXALGO may aggravate convulsions in patients with convulsive disorders, and all opioids may induce or aggravate seizures in some clinical settings.

5.11 Use in Pancreatic/Biliary Tract Disease

EXALGO can cause an increase in biliary tract pressure as a result of spasm in the sphincter of Oddi. Caution should be exercised in the administration of EXALGO to patients with inflammatory or obstructive bowel disorders, acute pancreatitis secondary to biliary tract disease and in patients about to undergo biliary surgery.

5.12 Driving and Operating Machinery

EXALGO may impair the mental and/or physical abilities needed to perform potentially hazardous activities such as driving a car or operating machinery. Caution patients accordingly. Also warn patients about the potential combined effects of EXALGO with other CNS depressants, including other opioids, phenothiazines, sedative/hypnotics, and alcohol [see Drug Interactions (7)].

5.13 Precipitation of Withdrawal

Mixed agonist/antagonist analgesics (i.e., pentazocine, nalbuphine, and butorphanol) should not be administered to patients who have received or are receiving a course of therapy with a pure opioid agonist analgesic, including EXALGO. In these patients, mixed agonists/antagonists analgesics may reduce the analgesic effect and/or may precipitate withdrawal symptoms. Do not abruptly discontinue EXALGO.

Clinical conditions or medicinal products that cause a sudden and significant shortening of gastrointestinal transit time may result in decreased hydromorphone absorption with EXALGO and may potentially lead to withdrawal symptoms in patients with a physical dependence on opioids.

6 ADVERSE REACTIONS

The following serious adverse reactions are discussed elsewhere in the labeling:

- Respiratory Depression [see Warnings and Precautions (5.3)]
- Head Injury and Increased Intracranial Pressure [see Warnings and Precautions (5.5)]
- Hypotensive Effect [see Warnings and Precautions (5.6)]
- Gastrointestinal Effects [see Warnings and Precautions (5.7)]
- Cardiac Arrest [see Overdosage (10)]
- Precipitation of Withdrawal [see Warnings and Precautions (5.13)]

6.1 Clinical Studies Experience

Because clinical trials are conducted under widely varying conditions, adverse reaction rates observed in the clinical trials of a drug cannot be directly compared to rates in the clinical trials of another drug and may not reflect the rates observed in clinical practice.

EXALGO was administered to a total of 2,524 patients in 15 controlled and uncontrolled clinical studies. Of these, 423 patients were exposed to EXALGO for greater than 6 months and 141 exposed for greater than one year.

The overall incidence of adverse reactions in patients greater than 65 years of age was higher, with a greater than 5% difference in rates for constipation and nausea when compared with younger patients. The overall incidence of adverse reactions in female patients was higher, with a greater than 5% difference in rates for nausea, vomiting, constipation and somnolence when compared with male patients.

A 12-week double-blind, placebo-controlled, randomized withdrawal study was conducted in opioid tolerant patients with moderate to severe low back pain [see Clinical Studies (14)]. A total of 447 patients were enrolled into the open-label titration phase with 268 patients randomized into the double-blind treatment phase. The adverse reactions that were reported in at least 2% of the patients are contained in Table 2.

Table 2. Number (%) of Patients with Adverse Reactions Reported in ≥2% of Patients with Moderate to Severe Low Back Pain During the Open-Label Titration Phase or Double-Blind Treatment Phase by Preferred Term
Preferred Term | Open-Label Titration Phase | Double-Blind Treatment Phase
 | EXALGO (N = 447) | EXALGO (N = 134) | Placebo (N = 134)
Constipation | 69 (15) | 10 (7) | 5 (4)
Nausea | 53 (12) | 12 (9) | 10 (7)
Somnolence | 39 (9) | 1 (1) | 0 (0)
Headache | 35 (8) | 7 (5) | 10 (7)
Vomiting | 29 (6) | 8 (6) | 6 (4)
Drug Withdrawal Syndrome | 22 (5) | 13 (10) | 16 (12)
Pruritus | 21 (5) | 1 (1) | 0 (0)
Dizziness | 17 (4) | 3 (2) | 2 (1)
Asthenia [Fatigue was grouped and reported with asthenia] | 16 (4) | 2 (1) | 6 (4)
Insomnia | 13 (3) | 7 (5) | 5 (4)
Diarrhea | 13 (3) | 5 (4) | 9 (7)
Back Pain | 13 (3) | 6 (4) | 8 (6)
Dry Mouth | 13 (3) | 2 (1) | 0 (0)
Edema Peripheral | 13 (3) | 3 (2) | 1 (1)
Hyperhidrosis | 13 (3) | 2 (1) | 2 (1)
Anorexia [Decreased appetite was grouped and reported with anorexia] | 10 (2) | 2 (1) | 0 (0)
Arthralgia | 9 (2) | 8 (6) | 3 (2)
Anxiety | 9 (2) | 0 (0) | 4 (3)
Abdominal pain [Abdominal pain upper was grouped and reported with abdominal pain] | 9 (2) | 4 (3) | 3 (2)
Muscle Spasms | 5 (1) | 3 (2) | 1 (1)
Weight Decreased | 3 (1) | 4 (3) | 3 (2)

The adverse reactions that were reported in at least 2% of the total treated patients (N=2,474) in the 14 chronic clinical trials are contained in Table 3.

Table 3. Number (%) of Patients with Adverse Reactions Reported in ≥2% of Patients with Chronic Pain Receiving EXALGO in 14 Clinical Studies by Preferred Term
Preferred Term | All Patients (N = 2,474)
Constipation | 765 (31)
Nausea | 684 (28)
Vomiting | 337 (14)
Somnolence | 367 (15)
Headache | 308 (12)
Asthenia [Fatigue was grouped and reported with asthenia] | 272 (11)
Dizziness | 262 (11)
Diarrhea | 201 (8)
Pruritus | 193 (8)
Insomnia | 161 (7)
Hyperhidrosis | 143 (6)
Edema Peripheral | 135 (5)
Anorexia [Decreased appetite was grouped and reported with anorexia] | 139 (6)
Dry Mouth | 121 (5)
Abdominal Pain [Abdominal pain upper was grouped and reported with abdominal pain] | 115 (5)
Anxiety | 95 (4)
Back Pain | 95 (4)
Dyspepsia [Reflux esophagitis, gastroesophageal reflux disease and Barrett's esophagus were grouped and reported with dyspepsia] | 88 (4)
Depression | 81 (3)
Dyspnea [Dyspnea exacerbated and dyspnea exertional were grouped and reported with dyspnea] | 76 (3)
Muscle Spasms | 74 (3)
Arthralgia | 72 (3)
Rash | 64 (3)
Pain in Extremity | 63 (3)
Pain | 58 (2)
Drug Withdrawal Syndrome | 55 (2)
Pyrexia | 52 (2)
Fall | 51 (2)
Chest discomfort [Chest pain and non-cardiac chest pain were grouped and reported with chest discomfort] | 51 (2)

The following Adverse Reactions occurred in patients with an overall frequency of <2% and are listed in descending order within each System Organ Class:

Cardiac disorders: palpitations, tachycardia, bradycardia, extrasystoles

Ear and labyrinth disorders: vertigo, tinnitus

Endocrine disorders: hypogonadism

Eye disorders: vision blurred, diplopia, dry eye, miosis

Gastrointestinal disorders: flatulence, dysphagia, hematochezia, abdominal distension, hemorrhoids, abnormal feces, intestinal obstruction, eructation, diverticulum, gastrointestinal motility disorder, large intestine perforation, anal fissure, bezoar, duodenitis, ileus, impaired gastric emptying, painful defecation

General disorders and administration site conditions: chills, malaise, feeling abnormal, feeling hot and cold, feeling jittery, hangover, difficulty in walking, feeling drunk, hypothermia

Infections and infestations: gastroenteritis, diverticulitis

Injury, poisoning and procedural complications: contusion, overdose

Investigations: weight decreased, hepatic enzyme increased, blood potassium decreased, blood amylase increased, blood testosterone decreased, oxygen saturation decreased

Metabolism and nutrition disorders: dehydration, fluid retention, increased appetite, hyperuricemia

Musculoskeletal and connective tissue disorders: myalgia

Nervous system disorders: tremor, sedation, hypoesthesia, paraesthesia, disturbance in attention, memory impairment, dysarthria, syncope, balance disorder, dysgeusia, depressed level of consciousness, coordination abnormal, hyperesthesia, myoclonus, dyskinesia, hyperreflexia, encephalopathy, cognitive disorder, convulsion, psychomotor hyperactivity

Psychiatric disorders: confusional state, nervousness, restlessness, abnormal dreams, mood altered, hallucination, panic attack, euphoric mood, paranoia, dysphoria, listless, crying, suicide ideation, libido decreased, aggression

Renal and urinary disorders: dysuria, urinary retention, urinary frequency, urinary hesitation, micturition disorder

Reproductive system and breast disorders: erectile dysfunction, sexual dysfunction

Respiratory, thoracic and mediastinal disorders: rhinorrhoea, respiratory distress, hypoxia, bronchospasm, sneezing, hyperventilation, respiratory depression

Skin and subcutaneous tissue disorders: erythema

Vascular disorders: flushing, hypertension, hypotension

7 DRUG INTERACTIONS

7.1 CNS Depressants

The concomitant use of EXALGO with central nervous system depressants such as hypnotics, sedatives, general anesthetics, antipsychotics and alcohol may cause additive depressant effects and respiratory depression. Additionally, hypotension and profound sedation or coma could occur. When this combination is indicated, the dose of one or both agents should be reduced. The concomitant use of alcohol should be avoided [see Clinical Pharmacology (12.3)].

7.2 Monoamine Oxidase (MAO) Inhibitors

MAO inhibitors may cause CNS excitation or depression, hypotension or hypertension if co-administered with opioids including EXALGO. EXALGO is not intended for patients taking MAO inhibitors or within 14 days of stopping such treatment.

7.3 Mixed Agonist/Antagonist Opioid Analgesics

The concomitant use of EXALGO with morphine agonist/antagonists (buprenorphone, nalbuphine, pentazocine) could lead to a reduction of the analgesic effect by competitive blocking of receptors, thus leading to risk of withdrawal symptoms. Therefore, this combination is not recommended.

7.4 Anticholinergics

Anticholinergics or other medications with anticholinergic activity when used concurrently with EXALGO may result in increased risk of urinary retention and/or severe constipation, which may lead to paralytic ileus.

7.5 Cytochrome P450 Enzymes

In vitro data suggest that hydromorphone in clinically relevant concentrations has minimal potential to inhibit the activity of human hepatic CYP450 enzymes including CYP1A2, 2C9, 2C19, 2D6, 3A4, and 4A11.

8 USE IN SPECIFIC POPULATIONS

8.1 Pregnancy

Teratogenic Effects
Pregnancy Category C: There are no adequate and well-controlled studies in pregnant women. Hydromorphone crosses the placenta. EXALGO should be used during pregnancy only if the potential benefit justifies the potential risk to the fetus [see Use in Specific Populations (8.2)].

Hydromorphone was not teratogenic in pregnant rats given oral doses up to 6.25 mg/kg/day or in pregnant rabbits administered oral doses up to 25 mg/kg/day during the period of organogenesis (~1.2 times the human exposure following 32 mg/day).

Hydromorphone administration to pregnant Syrian hamsters and CF-1 mice during major organ development revealed teratogenicity likely the result of maternal toxicity associated with sedation and hypoxia. In Syrian hamsters given single subcutaneous doses from 14 to 258 mg/kg during organogenesis (gestation days 8 to 10), doses ≥ 19 mg/kg hydromorphone produced skull malformations (exencephaly and cranioschisis). Continuous infusion of hydromorphone (5 mg/kg, s.c.) via implanted osmotic mini pumps during organogenesis (gestation days 7 to 10) produced soft tissue malformations (cryptorchidism, cleft palate, malformed ventricals and retina), and skeletal variations (supraoccipital, checkerboard and split sternebrae, delayed ossification of the paws and ectopic ossification sites). The malformations and variations observed in the hamsters and mice were at doses approximately three-fold higher and <one-fold lower, respectively, than a 32 mg human daily oral dose on a body surface area basis.

Nonteratogenic Effects
In the pre- and post-natal effects study in rats, neonatal viability was reduced at 6.25 mg/kg/day (~1.2 times the human exposure following 32 mg/day).

Neonates born to mothers who have been taking opioids regularly prior to delivery will be physically dependent. The withdrawal signs include irritability and excessive crying, tremors, hyperactive reflexes, increased respiratory rate, increased stools, sneezing, yawning, vomiting, and fever. The intensity of the syndrome does not always correlate with the duration of maternal opioid use or dose. There is no consensus on the best method of managing withdrawal. Approaches to the treatment of the syndrome have included supportive care and, if indicated, drugs such as paregoric or phenobarbital.

8.2 Labor and Delivery

EXALGO is not recommended for use in women during and immediately prior to labor and delivery. Administration of EXALGO to the mother shortly before delivery may result in some degree of respiratory depression in the neonate. However, neonates whose mothers received opioid analgesics during labor should be observed closely for signs of respiratory depression.

8.3 Nursing Mothers

Low concentrations of hydromorphone have been detected in human milk in clinical trials. Withdrawal symptoms can occur in breastfeeding infants when maternal administration of an opioid analgesic is stopped. Nursing should not be undertaken while a patient is receiving EXALGO since hydromorphone is excreted in the milk.

8.4 Pediatric Use

The safety and effectiveness of EXALGO in pediatric patients 17 years of age and younger have not been established.

8.5 Geriatric Use

Elderly patients have been shown to be more sensitive to the adverse effects of EXALGO compared to the younger population. Therefore, use extra caution when prescribing EXALGO in elderly patients and reduce the initial dose.

8.6 Neonatal Withdrawal Syndrome

Chronic maternal use of opiates or opioids during pregnancy coexposes the fetus. The newborn may experience subsequent neonatal withdrawal syndrome (NWS). Manifestations of NWS include irritability, hyperactivity, abnormal sleep pattern, high-pitched cry, tremor, vomiting, diarrhea, weight loss, and failure to gain weight. The onset, duration, and severity of the disorder differ based on such factors as the addictive drug used, time and amount of mother’s last dose, and rate of elimination of the drug from the newborn. Approaches to the treatment of this syndrome have included supportive care and, when indicated, drugs such as paregoric or phenobarbital.

8.7 Hepatic Impairment

In a study that used a single 4 mg oral dose of immediate-release hydromorphone tablets, four-fold increases in plasma levels of hydromorphone (Cmax and AUC0-∝) were observed in patients with moderate hepatic impairment (Child-Pugh Group B). Start patients with moderate hepatic impairment on a reduced dose and closely monitor during dose titration. The pharmacokinetics of hydromorphone in severe hepatic impairment patients have not been studied. Further increase in Cmax and AUC0-∝ of hydromorphone in this group is expected, therefore, use an even more conservative starting dose [see Dosage and Administration (2.4)].

8.8 Renal Impairment

Renal impairment affected the pharmacokinetics of hydromorphone and its metabolites following administration of a single 4 mg dose of immediate-release tablets. The effects of renal impairment on hydromorphone pharmacokinetics were two-fold and four-fold increases in plasma levels of hydromorphone (Cmax and AUC0-48h) in moderate (CLcr = 40 to 60 mL/min) and severe (CLcr < 30 mL/min) impairment, respectively. In addition, in patients with severe renal impairment hydromorphone appeared to be more slowly eliminated with longer terminal elimination half-life (40 hours) compared to subjects with normal renal function (15 hours). Start patients with moderate renal impairment on a reduced dose and closely monitor during dose titration. As EXALGO is only intended for once daily administration, consider use of an alternate analgesic that may permit more flexibility with the dosing interval in patients with severe renal impairment [see Dosage and Administration (2.4)].

9 DRUG ABUSE AND DEPENDENCE

9.1 Controlled Substance

EXALGO contains hydromorphone, a Schedule II controlled substance with a high potential for abuse similar to fentanyl, methadone, morphine, oxycodone, and oxymorphone. EXALGO can be abused and is subject to misuse, abuse, addiction, and criminal diversion [see Warnings and Precautions (5.2)]. The high drug content in the extended release formulation adds to the risk of adverse outcomes from abuse.

9.2 Abuse

All patients treated with opioids, including EXALGO, require careful monitoring for signs of abuse and addiction, because use of opioid analgesic products carries the risk of addiction even under appropriate medical use.

Addiction is a primary, chronic, neurobiologic disease, with genetic, psychosocial, and environmental factors influencing its development and manifestations. It is characterized by behaviors that include one or more of the following: impaired control over drug use, compulsive use, continued use despite harm, and craving.

"Drug-seeking" behavior is very common to addicts and drug abusers. Drug-seeking tactics include emergency calls or visits near the end of office hours, refusal to undergo appropriate examination, testing or referral, repeated claims of loss of prescriptions, tampering with prescriptions and reluctance to provide prior medical records or contact information for other treating physician(s). “Doctor shopping” (visiting multiple prescribers) to obtain additional prescriptions is common among drug abusers, people suffering from untreated addiction and criminals seeking drugs to sell.

Abuse and addiction are separate and distinct from physical dependence and tolerance. Physicians should be aware that addiction may not be accompanied by concurrent tolerance and symptoms of physical dependence in all addicts. In addition, abuse of opioids can occur in the absence of true addiction and is characterized by misuse for non-medical purposes, often in combination with other psychoactive substances. Since EXALGO may be diverted for non-medical use, careful record-keeping of prescribing information, including quantity, frequency, and renewal requests is strongly advised.

Proper assessment of the patient, proper prescribing practices, periodic re-evaluation of therapy, and proper dispensing and storage are appropriate measures that help to limit abuse of opioid drugs.

EXALGO is intended for oral use only. Misuse or abuse by breaking, crushing, chewing, or dissolving EXALGO poses a hazard of overdose and death. This risk is increased with concurrent abuse of EXALGO with alcohol and other substances.

With intravenous abuse, the tablet excipients, especially polyethylene oxide, can be expected to result in necrosis and inflammation of cardiac tissues. In addition, parenteral drug abuse is commonly associated with transmission of infectious disease such as hepatitis and HIV.

Healthcare professionals should contact their State Professional Licensing Board or State Controlled Substances Authority for information on how to prevent and detect abuse or diversion of this product.

9.3 Dependence

Tolerance is a state of adaptation in which exposure to a drug induces changes that result in a diminution of one or more of the drug’s effects over time. Tolerance could occur to both the desired and undesired effects of drugs, and may develop at different rates for different effects.

Physical dependence is a state of adaptation that is manifested by an opioid specific withdrawal syndrome that can be produced by abrupt cessation, rapid dose reduction, decreasing blood level of the drug, and/or administration of an antagonist. The opioid abstinence or withdrawal syndrome is characterized by some or all of the following: restlessness, lacrimation, rhinorrhea, yawning, perspiration, chills, piloerection, myalgia, mydriasis, irritability, anxiety, backache, joint pain, weakness, abdominal cramps, insomnia, nausea, anorexia, vomiting, diarrhea, increased blood pressure, respiratory rate, or heart rate.

Infants born to mothers physically dependent on opioids will also be physically dependent and may exhibit respiratory difficulties and withdrawal symptoms [see Use in Specific Populations (8.1, 8.2)].

10 OVERDOSAGE

10.1 Symptoms

Acute overdosage with opioids can be manifested by respiratory depression, somnolence progressing to stupor or coma, skeletal muscle flaccidity, cold and clammy skin, constricted pupils, and sometimes bradycardia, hypotension and death. The extended release characteristics of EXALGO should also be taken into account when treating the overdose. Even in the face of improvement, continued medical monitoring is required because of the possibility of extended effects. Deaths due to overdose could occur with abuse and misuse of EXALGO.

Due to the delayed mean apparent peak plasma level of EXALGO occurring at 16 hours following administration as well as the 11 hour mean elimination half-life of EXALGO, patients who receive an overdose will require an extended period of monitoring and treatment that may go beyond 24 to 48 hours.

10.2 Treatment

Give primary attention to the re-establishment of a patent airway and institution of assisted or controlled ventilation. Employ supportive measures (including oxygen and vasopressors) in the management of circulatory shock and pulmonary edema accompanying overdose as indicated. Cardiac arrest or arrhythmias will require advanced life support techniques.

The pure opioid antagonists, such as naloxone and naltrexone are specific antidotes to respiratory depression from opioid overdose. Since the duration of reversal would be expected to be less than the duration of action of hydromorphone in EXALGO, the patient must be carefully monitored until spontaneous respiration is reliably re-established. EXALGO will continue to release and add to the hydromorphone load for up to 24 hours after administration and the management of an overdose should be monitored accordingly, at least 24 to 48 hours beyond the overdose.

Only administer opioid antagonists in the presence of clinically significant respiratory or circulatory depression secondary to hydromorphone overdose. In patients who are physically dependent on any opioid agonist including EXALGO, an abrupt or complete reversal of opioid effects may precipitate an acute abstinence syndrome. The severity of the withdrawal syndrome produced will depend on the degree of physical dependence and the dose of the antagonist administered. Please see the prescribing information for the specific opioid antagonist for details of their proper use.

11 DESCRIPTION

EXALGO tablets contain hydromorphone hydrochloride, a mu-opioid agonist.

Hydromorphone hydrochloride USP is 4,5α-epoxy-3-hydroxy-17-methlymorphinan-6-one hydrochloride. Hydromorphone hydrochloride is a white or almost white crystalline powder that is freely soluble in water, very slightly soluble in ethanol (96%), and practically insoluble in methylene chloride. Its empirical formula is C17H19NO3•HCl. The compound has the following structural formula:

EXALGO also contains the following inactive ingredients: butylated hydroxytoluene, cellulose acetate, iron oxide black, ferric oxide red (8 mg only), ferric oxide yellow (12 mg and 16 mg only), hypromellose, lactose anhydrous, lactose monohydrate, magnesium stearate, polyethylene glycol, polyethylene oxide, povidone, sodium chloride, titanium dioxide, and triacetin.

12 CLINICAL PHARMACOLOGY

12.1 Mechanism of Action

Hydromorphone, a semi-synthetic morphine derivative, is a hydrogenated ketone of morphine. Hydromorphone is principally an agonist of mu-receptors, showing a weak affinity for k-receptors. Comparing relative binding affinity for mu- and k-opioid receptors, hydromorphone binds more specifically to mu-receptors than structurally related morphine. As an opioid agonist, the principle therapeutic action of hydromorphone is analgesia. The precise mechanism of action of opioid analgesics is not known but the effects are thought to be mediated through opioid-specific receptors located predominantly in the central nervous system (CNS). Interaction with the mu-opioid receptor subtype is believed to be responsible for most of hydromorphone’s clinical effects. There is no intrinsic limit to the analgesic effect of hydromorphone. Clinically, however, dosage limitations are imposed by the adverse effects, primarily respiratory depression, sedation, nausea, and vomiting, which can result from high doses.

12.2 Pharmacodynamics

Hydromorphone exerts its principal pharmacological effects on the CNS and smooth muscle, including the gastrointestinal tract. These effects are expressed and modulated by binding to specific opioid receptors. Hydromorphone is principally an agonist of mu-receptors, showing a weak affinity for k-receptors. Analgesia occurs as a consequence of the binding of hydromorphone to the mu-receptors of the CNS. Although estimates vary (from 2 to 10 times), oral hydromorphone appears to be approximately 5 times as potent (by weight) as morphine. Respiratory depression occurs principally by direct action on the cerebral respiratory control centers. Hydromorphone may cause nausea and vomiting due to direct stimulation of the chemoreceptor for emesis in the posterior area of the medulla.

Central Nervous System
Hydromorphone produces dose-related respiratory depression by direct action on brain stem respiratory centers. The respiratory depression involves a reduction in the responsiveness of the brain stem respiratory centers to increases in carbon dioxide tension and to electrical stimulation.

Hydromorphone depresses the cough reflex by direct effect on the cough center in the medulla.

Hydromorphone causes miosis, even in total darkness. Pinpoint pupils are a sign of opioid overdose but are not pathognomic. Marked mydriasis, rather than miosis, may be seen due to severe hypoxia in overdose situations.

Gastrointestinal Tract and Other Smooth Muscle
Hydromorphone decreases gastric, biliary and pancreatic secretions, and causes a reduction in motility associated with an increase in smooth muscle tone in the antrum of the stomach and duodenum. Digestion of food in the small intestine is delayed and propulsive contractions are decreased. Propulsive peristaltic waves in the colon are decreased, while tone may be increased to the point of spasm resulting in constipation. Hydromorphone also can cause an increase in bilary tract pressure as a result of spasm of the sphincter of Oddi.

Cardiovascular System
Hydromorphone may produce peripheral vasodilation which may result in orthostatic hypotension. Release of histamine may occur with or without associated peripheral vasodilation. Manifestations of histamine release and/or peripheral vasodilation may include pruritus, flushing, red eyes, and sweating.

Endocrine System
Opioid agonists have been shown to have a variety of effects on the secretion of hormones. Opioids inhibit the secretion of adrenocorticotropic hormone (ACTH), cortisol, and luteinizing hormone (LH) in humans. They also stimulate prolactin, growth hormone (GH) secretion, and pancreatic secretion of insulin and glucagon in humans and other species, rats and dogs. Thyroid stimulating hormone (TSH) has been shown to be both inhibited and stimulated by opioids.

12.3 Pharmacokinetics

Absorption
EXALGO is an extended release formulation of hydromorphone that produces a gradual increase in hydromorphone concentrations. Following a single dose administration of EXALGO, plasma concentrations gradually increase over 6 to 8 hours, and thereafter concentrations are sustained for approximately 18 to 24 hours post-dose. The median Tmax values ranged from 12 to 16 hours. The mean half-life was approximately 11 hours, ranging from 8 to 15 hours in most individual subjects. Linear pharmacokinetics has been demonstrated for EXALGO over the dose range 8 to 64 mg, with a dose-proportional increase in Cmax and overall exposure (AUC0-∝) (see Table 4). Steady-state plasma concentrations are approximately twice those observed following the first dose, and steady state is reached after 3 to 4 days of once-daily dosing of EXALGO. At steady state, EXALGO given once daily maintained hydromorphone plasma concentrations within the same concentration range as the immediate-release tablet given 4 times daily at the same total daily dose, and diminished the fluctuations between peak and trough concentrations seen with the immediate-release tablet (see Figure 1). The bioavailability of EXALGO once daily and immediate-release hydromorphone four times daily in adults is comparable as presented in Table 4.

Figure 1. Mean Steady-State Plasma Concentration Profile

Table 4: Mean (±SD) EXALGO Pharmacokinetic Parameters
Regimen | Dosage | Tmax [Median (range) reported for Tmax] (hrs) | Cmax(ng/mL) | AUC (ng•hr/mL) | T½ (hr)
Single Dose (N = 31) | 8 mg | 12 (4-30) | 0.93 (1.01) | 18.1 (5.8) | 10.6 (4.3)
Single Dose (N = 31) | 16 mg | 16 (6-30) | 1.69 (0.78) | 36.5 (11.3) | 10.3 (2.4)
Single Dose (N = 31) | 32 mg | 16 (4-24) | 3.25 (1.37) | 72.2 (24.3) | 11.0 (3.2)
Single Dose (N = 31) | 64 mg | 16 (6-30) | 6.61 (1.75) | 156.0 (30.6) | 10.9 (3.8)
Multiple Dose [Steady-state results on Day 5 (0-24 hours)] (N = 29) | 16 mg q24h | 12 (6-24) | 3.54 (0.96) [Cmin 2.15 (0.87) ng/mL] | 57.6 (16.3) | NA
Multiple Dose [Steady-state results on Day 5 (0-24 hours)] (N = 29) | IR 4 mg q6h | 0.75 (0.5-2) | 5.28 (1.37) [Cmin 1.47 (0.42) ng/mL] | 54.8 (14.8) | NA
NA = not applicable

Food Effect
The pharmacokinetics of EXALGO are not affected by food as indicated by bioequivalence when administered under fed and fasting conditions. Therefore, EXALGO may be administered without regard to meals. When a 16 mg dose of EXALGO was administered to healthy volunteers immediately following a high-fat meal, the median time to Cmax (Tmax) was minimally affected by the high-fat meal occurring at 16 hours compared to 18 hours while fasting.

Alcohol Effect
An in vivo study examined the effect of alcohol (40%, 20%, 4% and 0%) on the bioavailability of a single dose of 16 mg of EXALGO in healthy, fasted or fed volunteers. The results showed that the hydromorphone mean AUC0-∝ was 5% higher and 4% lower (not statistically significant) in the fasted and fed groups respectively after co-administration of 240 mL of 40% alcohol. The AUC0-∝ was similarly unaffected in subjects following the co-administration of EXALGO and alcohol (240 mL of 20% or 4% alcohol).

The change in geometric mean Cmax with concomitant administration of alcohol and EXALGO ranged from an increase of 10% to 31% across all conditions studied. The change in mean Cmax was greater in the fasted group of subjects. Following concomitant administration of 240 mL of 40% alcohol while fasting the mean Cmax increased by 37%, and up to 151% in an individual subject. Following the concomitant administration of 240 mL of 20% alcohol while fasting the mean Cmax increased by 35% and up to 139% in an individual subject. Following the concomitant administration of 240 mL of 4% alcohol while fasting the mean Cmax increased by 19% on average and as much as 73% for an individual subject. The range of median Tmax for the fed and fasted treatments with 4%, 20% and 40% alcohol was 12 to 16 hours compared to 16 hours for the 0% alcohol treatments.

Distribution
Following intravenous administration of hydromorphone to healthy volunteers, the mean volume of distribution was 2.9 (±1.3) L/kg, suggesting extensive tissue distribution. The mean extent of binding of hydromorphone to human plasma proteins was determined to be 27% in an in vitro study.

Metabolism
After oral administration of an immediate-release formulation, hydromorphone undergoes extensive first-pass metabolism and is metabolized primarily in the liver by glucuronidation to hydromorphone-3-glucuronide, which follows a similar time course to hydromorphone in plasma. Exposure to the glucuronide metabolite is 35 to 40 times higher than exposure to the parent drug.

Excretion
Approximately 75% of the administered dose is excreted in urine. Most of the administered hydromorphone dose is excreted as metabolites. Approximately 7% and 1% of the dose are excreted as unchanged hydromorphone in urine and feces, respectively.

Special Populations
Geriatric - Age has no effect on the pharmacokinetics of hydromorphone based on the data obtained from an immediate release product.

Gender - Females appeared to have approximately 10% higher mean systemic exposure in terms of Cmax and AUC values.

Race - The effect of race on EXALGO pharmacokinetics has not been studied.

Pediatric - Pharmacokinetics of EXALGO were not evaluated in the pediatric population.

Hepatic Impairment - In a study that used a single 4 mg oral dose of immediate-release hydromorphone tablets, four-fold increases in plasma levels of hydromorphone (Cmax and AUC0-∝) were observed in patients with moderate hepatic impairment (Child-Pugh Group B). Pharmacokinetics of hydromorphone in severe hepatic impairment patients has not been studied. Further increase in Cmax and AUC0-∝ of hydromorphone in this group is expected. Start patients with moderate and severe hepatic impairment on a reduced dose of EXALGO and closely monitor during dose titration [see Dosage and Administration (2.4) and Specific Populations (8.7)].

Renal Impairment - Renal impairment affected the pharmacokinetics of hydromorphone and its metabolites following administration of a single 4 mg dose of immediate-release tablets. The effects of renal impairment on hydromorphone pharmacokinetics were two-fold and four-fold increases in plasma levels of hydromorphone (Cmax and AUC0-48h) in moderate (CLcr = 40 to 60 mL/min) and severe (CLcr < 30 mL/min) impairment, respectively. In addition, in patients with severe renal impairment hydromorphone appeared to be more slowly eliminated with longer terminal elimination half-life (40 hr) compared to subjects with normal renal function (15 hr). Start patients with moderate renal impairment on a reduced dose of EXALGO and closely monitored during dose titration. As EXALGO is only intended for once-daily administration, consider use of an alternate analgesic that may permit more flexibility with the dosing interval in patients with severe renal impairment [see Dosage and Administration (2.4) and Use in Specific Populations (8.8)].

13 NONCLINICAL TOXICOLOGY

13.1 Carcinogenesis, Mutagenesis, Impairment of Fertility

Carcinogenesis
Long-term studies in animals to evaluate the carcinogenic potential of hydromorphone hydrochloride have not been conducted.

Mutagenesis
Hydromorphone was not mutagenic in the in vitro bacterial reverse mutation assay (Ames assay). Hydromorphone was not clastogenic in either the in vitro human lymphocyte chromosome aberration assay or the in vivo mouse micronucleus assay.

Impairment of Fertility
Hydromorphone given orally to rats during the mating period caused a slight but statistically significant reduction in implantations at 6.25 mg/kg/day (~1.2 times the human exposure following to 32 mg/day).

14 CLINICAL STUDIES

EXALGO was investigated in a double-blind, placebo-controlled, randomized withdrawal study in opioid tolerant patients with moderate-to-severe low back pain. Patients were considered opioid tolerant if they were currently on opioid therapy that was ≥60 mg/day of oral morphine equivalent for at least 2 months prior to screening. Patients entered an open-label conversion and titration phase with EXALGO, were converted to a starting dose that was approximately 75% of their total daily morphine equivalent dose, and were dosed once daily until adequate pain control was achieved while exhibiting tolerable side effects. Supplemental immediate-release hydromorphone tablets were allowed throughout the study. Patients who achieved a stable dose entered a 12-week, double-blind, placebo-controlled, randomized treatment phase. Mean daily dose at randomization was 37.8 mg/day (range of 12 mg/day to 64 mg/day). Fifty-eight (58) percent of patients were successfully titrated to a stable dose of EXALGO during the open-label conversion and titration phase.

During the double-blind treatment phase, patients randomized to EXALGO continued with the stable dose achieved in the conversion and titration phase of the study. Patients randomized to placebo received, in a blinded manner, EXALGO and matching placebo in doses tapering from the stable dose achieved in conversion and titration. During the taper down period, patients were allowed immediate-release hydromorphone tablets as supplemental analgesia to minimize opioid withdrawal symptoms in placebo patients. After the taper period, the number of immediate-release hydromorphone tablets was limited to two tablets per day. Forty-nine (49) percent of patients treated with EXALGO and 33% of patients treated with placebo completed the 12-week treatment period.

EXALGO provided superior analgesia compared to placebo. There was a significant difference between the mean changes from Baseline to Week 12 or Final Visit in average weekly pain intensity Numeric Rating Scale (NRS) scores obtained from patient diaries between the two groups. The proportion of patients with various degrees of improvement from screening to Week 12 or Final Visit is shown in Figure 2. For this analysis, patients who discontinued treatment for any reason prior to Week 12 were assigned a value of zero improvement.

Figure 2. Percent Reduction in Average Pain Intensity from Screening to Week 12 or Final Visit

16 HOW SUPPLIED/STORAGE AND HANDLING

16.1 Storage and Handling

EXALGO contains hydromorphone which is a controlled substance. Like fentanyl, methadone, morphine, oxycodone, and oxymorphone, hydromorphone is controlled under Schedule II of the Federal Controlled Substances Act. EXALGO may be targeted for theft and diversion by criminals [see Warnings and Precautions (5)]. For further information on this product, healthcare professionals can contact a medical information specialist at Covidien at 1-800-778-7898.

Store at 25ºC (77ºF); excursions permitted to 15° to 30°C (59° to 86°F) [See USP Controlled Room Temperature].

16.2 Disposal of EXALGO

Patients and members of their household must be advised to dispose of any tablets remaining from a prescription as soon as they are no longer needed. Information is available in the Medication Guide. To dispose of unused EXALGO flush all remaining tablets down the toilet.

16.3 How Supplied

EXALGO Tablet Strengths
Strength | Color | Tablet Description | Bottle Count | NDC
8 mg | Red | Round, biconvex, printed with “EXH 8” | 100 | 23635-408-01
12 mg | Dark yellow | Round, biconvex, printed with “EXH 12” | 100 | 23635-412-01
16 mg | Yellow | Round, biconvex, printed with “EXH 16” | 100 | 23635-416-01

17 PATIENT COUNSELING INFORMATION

17.1 Safe Use

Before initiating treatment with EXALGO, explain the points listed below to caregivers and patients. Instruct patients to read the Medication Guide each time EXALGO is dispensed because new information may be available.

- Advise patients that EXALGO is for use only in patients who are already receiving opioid pain medicine and their body is used to taking these medications.
- Advise patients that EXALGO contains hydromorphone, and should be taken only as directed.
- Advise patients that EXALGO must be swallowed whole. The extended release tablets may release all their contents at once if broken, chewed, crushed, or dissolved resulting in risk of fatal overdose of hydromorphone.
- Advise patients not to take another dose of EXALGO within 24 hours.
- Advise patients never to change the dose of EXALGO without first consulting their healthcare provider. Individualization of dosage is essential to make optimal use of this medication. Advise patients regarding the need to contact their healthcare provider if pain control is inadequate and to report episodes of breakthrough pain and adverse experiences occurring during therapy to their healthcare provider.
- Advise patients to keep EXALGO tablets in a secure place out of the reach of children. Accidental consumption of EXALGO, especially in children, can result in a fatal overdose of hydromorphone.
- Advise patients that EXALGO must not be given to anyone other than the individual for whom it was prescribed. Instruct patients against use by individuals other than the patient for whom it was prescribed, as such inappropriate use may have severe medical consequences, including death.

17.2 Risk of Gastrointestinal Obstruction

Advise patients that people with certain stomach or intestinal problems such as narrowing of the intestines or previous surgery may be at higher risk of developing a blockage. Symptoms include abdominal distension, abdominal pain, severe constipation, or vomiting. Instruct patients to contact their healthcare provider immediately if they develop these symptoms.

17.3 Mental and/or Physical Ability

Caution patients that EXALGO may cause drowsiness, dizziness, or lightheadedness, and may impair mental and/or physical abilities required for the performance of potentially hazardous tasks, such as driving a car or operating machinery.

17.4 Avoidance of Alcohol or Other CNS Depressants

Advise patients not to combine EXALGO with other pain medications, sleep aids, or tranquilizers except by the orders of a healthcare professional, and not to consume alcohol while taking EXALGO, because dangerous additive effects could occur, resulting in serious injury or death.

17.5 Pregnancy

Advise women of childbearing potential who become, or who plan to become, pregnant to consult their healthcare professional regarding the effects of EXALGO and other drug use during pregnancy on themselves and their unborn child. Advise women that EXALGO can pass through breast milk and may cause serious harm to a nursing infant so they should not breastfeed while taking EXALGO.

17.6 Cessation of Therapy

Advise patients that if they have been receiving treatment with EXALGO for more than a few days to weeks and the medicine is no longer needed, it is important to taper the dose and that abruptly discontinuing the medication could cause withdrawal symptoms. Provide patients with a dose schedule to accomplish a gradual discontinuation of the medication.

Advise patients that if they stop taking this medication for 3 or more days, to contact their healthcare professional before restarting their medication, to avoid complications of being opioid non-tolerant.

17.7 Drug of Abuse

Advise patients that the active ingredient in EXALGO is hydromorphone, which is a drug that some people abuse. EXALGO must be taken only by the patient for whom it was prescribed, and it must be protected from theft or misuse in the work or home environment.

17.8 Constipation

Advise patients that taking EXALGO has the potential to cause severe constipation. Consider the use of appropriate laxatives and/or stool softeners and other therapeutic approaches with the initiation of EXALGO therapy.

Advise patients that the drug is contained within a non-absorbable shell designed to release the drug at a controlled rate. The tablet shell is eliminated from the body and patients should not be alarmed if they occasionally notice something that looks like a tablet in their stool.

17.9 Storage/Destruction of Unused Tablets

Advise patients that when EXALGO is no longer needed to flush the unused tablets down the toilet.

17.10 FDA-Approved Patient Labeling

MEDICATION GUIDE
EXALGO® (eks-al-goh)
(hydromorphone HCl) Extended-Release Tablets CII

IMPORTANT:
Keep EXALGO in a safe place away from children. Accidental use by a child is a medical emergency and can result in death. If a child accidentally takes EXALGO, get emergency help right away, even if the child is not having any side effects.

Read the Medication Guide that comes with EXALGO before you start taking it and each time you get a new prescription. There may be new information. This Medication Guide does not take the place of talking to your healthcare provider about your medical condition or your treatment. Share this important information with members of your household.

What is the most important information I should know about EXALGO?

1. EXALGO overdose can cause life threatening breathing problems that can lead to death.

- Do not take EXALGO unless you are already regularly using opioid pain medicines around-the-clock and your body is used to taking these medicines. This means you are opioid tolerant.
- Take EXALGO exactly as prescribed by your healthcare provider. Do not take more than your prescribed daily dose. It is important that you do not take another dose of EXALGO within 24 hours.
- Swallow the EXALGO tablet whole. Do not break, chew, crush, or dissolve EXALGO before swallowing, or inject the contents. You could receive the full daily dose of medicine too fast. This is very dangerous. It may cause you to have trouble breathing, and lead to death. If you cannot swallow EXALGO whole, tell your healthcare provider. You will need a different pain medicine.
- EXALGO is not for use to treat pain that you only have once in a while (“as-needed”).
- EXALGO is not for use for short-term pain relief from injuries or surgery.
- It is important for you to stay under the care of your healthcare provider while taking EXALGO.

2. Prevent theft, misuse, or abuse. Keep EXALGO in a safe place to protect it from being stolen. EXALGO can be a target for people who misuse or abuse prescription medicines or street drugs.

3. Never give EXALGO to anyone else, even if they have the same symptoms you have. It may harm them or cause death. Selling or giving away this medicine is against the law.

What is EXALGO?

- EXALGO is a prescription medicine that contains the opioid (narcotic) pain medicine hydromorphone. The medicine in EXALGO is slowly released over 24 hours. If you break, chew, crush, or dissolve EXALGO before swallowing, or inject the contents, the hydromorphone hydrochloride may be released too fast and you may overdose (see What is the most important information I should know about EXALGO?).
- EXALGO is a strong opioid pain medicine. EXALGO is used in people who are opioid tolerant, to manage moderate to severe pain that continues around-the-clock and is expected to last for a long period of time.
- EXALGO is a federally controlled substance (CII) because it contains a strong opioid pain medicine that can be a target for people who abuse prescription medicines or street drugs.

Who should not take EXALGO?

Do not take EXALGO if you:

- are not already regularly taking opioid pain medicine and your body is not used to taking these medicines for your pain. This means you are not opioid tolerant.
- are having an asthma attack or have severe asthma, trouble breathing, or certain other lung problems.
- have a bowel blockage called paralytic ileus.
- have narrowing of the stomach or intestines, or have had surgery to your stomach or intestines.
- are allergic to any of the ingredients in EXALGO or to medicines that contain sulfite. See the end of this Medication Guide for a complete list of the ingredients in EXALGO.

Talk to your healthcare provider before taking this medicine if you have any of the conditions listed above.

What should I tell my healthcare provider before starting EXALGO?

EXALGO may not be right for you. Before taking EXALGO, tell your healthcare provider if you:

- have trouble breathing or lung problems such as asthma, wheezing, or shortness of breath.
- have had a head injury or brain problem.
- have liver or kidney problems.
- have an adrenal gland problem, such as Addison’s disease.
- have thyroid problems.
- have seizures (convulsions or fits).
- have problems with your pancreas or gallbladder.
- have constipation.
- have had stomach or intestinal surgery, or a blockage in your stomach or intestine.
- have prostate enlargement or problems urinating.
- have low blood pressure.
- have mental problems including depression, anxiety, or hallucinations (seeing or hearing things that are not there).
- have or had a drinking problem or alcoholism, or a family history of this problem.
- have or had a drug abuse or addiction problem in the past, or a family history of this problem.
- have any other medical conditions.
- are pregnant or planning to become pregnant. If you take EXALGO regularly before your baby is born, your newborn baby may have withdrawal symptoms because their body has become used to the medicine. Symptoms of withdrawal in a newborn baby may include:
  - irritability
  - crying more than usual
  - shaking (tremors)
  - jitteriness
  - breathing faster than normal
  - diarrhea or more stools than normal
  - vomiting
  - fever
  If you take EXALGO right before your baby is born, your baby could have breathing problems.
- are breastfeeding. Do not breastfeed while taking EXALGO. Some EXALGO passes into breast milk. A nursing baby could become drowsy or have difficulty breathing or feeding well. If you stop breastfeeding or suddenly stop taking EXALGO while breastfeeding, your baby may have withdrawal symptoms. See the list of withdrawal symptoms above.

Tell your healthcare provider about all the medicines you take, including prescription and non-prescription medicines, vitamins, and herbal supplements. Some medicines may cause serious or life-threatening medical problems when taken with EXALGO. Sometimes, the doses of certain medicines and EXALGO need to be changed if used together. Be especially careful about other medicines that make you sleepy such as:

- other pain medicines
- antidepressant medicines
- sleeping pills
- antihistamines
- anti-anxiety medicines
- muscle relaxants
- anti-nausea medicines
- tranquilizers

Do not take EXALGO if you already take a monoamine oxidase (MAO) inhibitor medicine or within 14 days after you stop taking an MAO inhibitor medicine.

Do not take any new medicine while using EXALGO until you have talked to your healthcare provider or pharmacist. They will tell you if it is safe to take other medicines while you are taking EXALGO. Ask your healthcare provider if you are not sure if your medicine is one listed above.

Know the medicines you take. Keep a list of them to show your healthcare provider and pharmacist when you get a new medicine.

How should I take EXALGO?

- Take EXALGO exactly as prescribed by your healthcare provider. Do not change your dose unless your healthcare provider tells you to.
- Take EXALGO one time each day at the same time every day.
- Swallow the EXALGO tablet whole. Do not break, chew, crush, or dissolve EXALGO before swallowing, or inject the contents of EXALGO (see What is the most important information I should know about EXALGO?). Tell your healthcare provider if you cannot swallow EXALGO whole. You will need to take a different pain medicine.
- EXALGO can be taken with or without food.
- The EXALGO tablet is contained in a hard shell that does not dissolve in your body. The tablet shell passes through your body in your stool. You may notice something that looks like a tablet in your bowel movement. This is normal.
- Call your healthcare provider if the dose of EXALGO that you are taking does not control your pain.
- If you stop taking EXALGO for 3 or more days, call your healthcare provider before restarting the medicine.
- If you are not sure if you have taken your dose, do not take another dose. Taking more EXALGO than prescribed may cause you to overdose. If you are not sure what to do, call your healthcare provider.
- If you take too much EXALGO or overdose, call 911 or get emergency help right away.
- Do not stop taking EXALGO without talking to your healthcare provider. Opioid medicines such as EXALGO can cause physical dependence. You should not suddenly stop taking EXALGO because you may become sick with uncomfortable withdrawal symptoms. If your healthcare provider decides you no longer need EXALGO, ask how to slowly stop taking this medicine to avoid uncomfortable withdrawal symptoms.

What should I avoid while taking EXALGO?

- Do not drive or operate heavy machinery, or do other dangerous activities, until you know how EXALGO affects how alert you are. EXALGO can make you sleepy, and cause you to feel dizzy or lightheaded. This may affect your ability to think and react. Ask your healthcare provider when it is okay to do these activities.
- Do not drink alcohol or use prescription or non-prescription medicines that contain alcohol while taking EXALGO. Using alcohol while taking EXALGO may cause you to overdose and die.

What are the possible side effects of EXALGO?

EXALGO can cause serious side effects that can lead to death (see What is the most important information I should know about EXALGO?).

Call your healthcare provider or get emergency medical help if you:

- have trouble breathing.
- have extreme drowsiness with slowed breathing.
- have shallow breathing (little chest movement with breathing).
- feel faint, dizzy, confused, or have other unusual symptoms.

These can be symptoms that you have taken too much (overdose) EXALGO or the dose is too high for you. These symptoms may lead to serious problems or death if not treated right away.

Drop in your blood pressure. This can make you feel dizzy if you get up too fast from sitting or lying down. Low blood pressure is also more likely to happen if you take other medicines that can also lower your blood pressure. Severe low blood pressure can happen if you lose blood or take certain other medicines.

Symptoms of stomach or intestinal blockage. EXALGO tablets do not change shape when they pass through your stomach and intestine. People who have certain stomach or intestinal problems, such as narrowing (stricture), or who have had surgery in these areas may get symptoms of a blockage. Tell your healthcare provider right away if you get any of these symptoms:

- vomiting
- severe constipation
- abdominal pain
- abdominal distension

Allergic reactions. EXALGO contains sodium metabisulfite, a sulfite that may cause allergic-type reactions. Symptoms of an allergic reaction to EXALGO and sulfites may include:

- feel dizzy or faint
- trouble breathing
- pounding heart beat
- chest pain
- swelling of the face, throat, or tongue
- feeling of doom

Physical dependence. Stopping EXALGO suddenly can make you sick with withdrawal symptoms because your body has become used to it. Talk to your healthcare provider about slowly stopping EXALGO. Physical dependence is not the same thing as addiction. Tell your healthcare provider if you have any of the following symptoms of withdrawal while slowly stopping EXALGO:

- feel restless
- tearing eyes
- runny nose
- yawning
- sweating
- chills or hair on your arms “standing up”
- muscle aches, backache, joint pain
- weakness
- dilated pupils of your eyes
- feel irritable or anxious
- nausea, loss of appetite, vomiting, diarrhea
- increase in your blood pressure, breathing faster, or your heart beats faster
- sleep problems

There is a chance of abuse or addiction with EXALGO. The chance is higher if you are, or have been addicted to or abused other medicines, street drugs, or alcohol, or if you have a history of mental problems.

The most common side effects of EXALGO include:

- constipation
- nausea
- drowsiness or sleepiness
- headache
- vomiting
- tiredness
- dizziness

Constipation (not enough or hard bowel movements) is a common side effect of pain medicines (opioids) including EXALGO and is unlikely to go away without treatment. Talk to your healthcare provider about dietary changes, the use of laxatives (medicines to treat constipation) and stool softeners to prevent or treat constipation while taking EXALGO.

These are not all the possible side effects of EXALGO. Talk to your healthcare provider if you have any side effects that bother you or do not go away.

Call your doctor for medical advice about side effects. You may report side effects to FDA at 1-800-FDA-1088.

How should I store EXALGO?

- Store EXALGO at 59° to 86°F (15° to 30°C).
- Keep EXALGO in the container it comes in.
- Keep EXALGO dry and away from heat.
- After you stop taking EXALGO flush any unused tablets down the toilet.

Keep EXALGO in a safe and secure place away from children.

General information about EXALGO

Medicines are sometimes prescribed for purposes other than those listed in a Medication Guide. Do not use EXALGO for a purpose for which it was not prescribed. Do not give EXALGO to other people, even if they have the same symptoms you have. EXALGO can harm other people and even cause death. Sharing EXALGO is against the law.

This Medication Guide summarizes the most important information about EXALGO. If you would like more information, talk with your healthcare provider. You can ask your pharmacist or healthcare provider for information about EXALGO that is written for healthcare professionals.

For further information or to report suspected adverse reactions, go to www.exalgo.com or contact Covidien at 1-800-778-7898.

What are the ingredients of EXALGO?

- Active Ingredient: hydromorphone hydrochloride.
- Inactive Ingredients: butylated hydroxytoluene, cellulose acetate, iron oxide black, hypromellose, lactose anhydrous, lactose monohydrate, magnesium stearate, polyethylene glycol, polyethylene oxide, povidone, sodium chloride, titanium dioxide and triacetin. The 8 mg tablets also contain ferric oxide red. The 12 and 16 mg tablets also contain ferric oxide yellow.

This Medication Guide has been approved by the U.S. Food and Drug Administration.

OROS is a registered trademark of ALZA Corporation.
EXALGO is a registered trademark of Mallinckrodt Inc.
COVIDIEN, COVIDIEN with logo and Covidien logo are U.S. and/or internationally registered trademarks of Covidien AG.

© 2010 Mallinckrodt Inc., a Covidien company

Distributed by:
Mallinckrodt Brand Pharmaceuticals, Inc.
Hazelwood, MO 63042 USA

Issued 11/2010

10206402

Mallinckrodt
COVIDIEN™